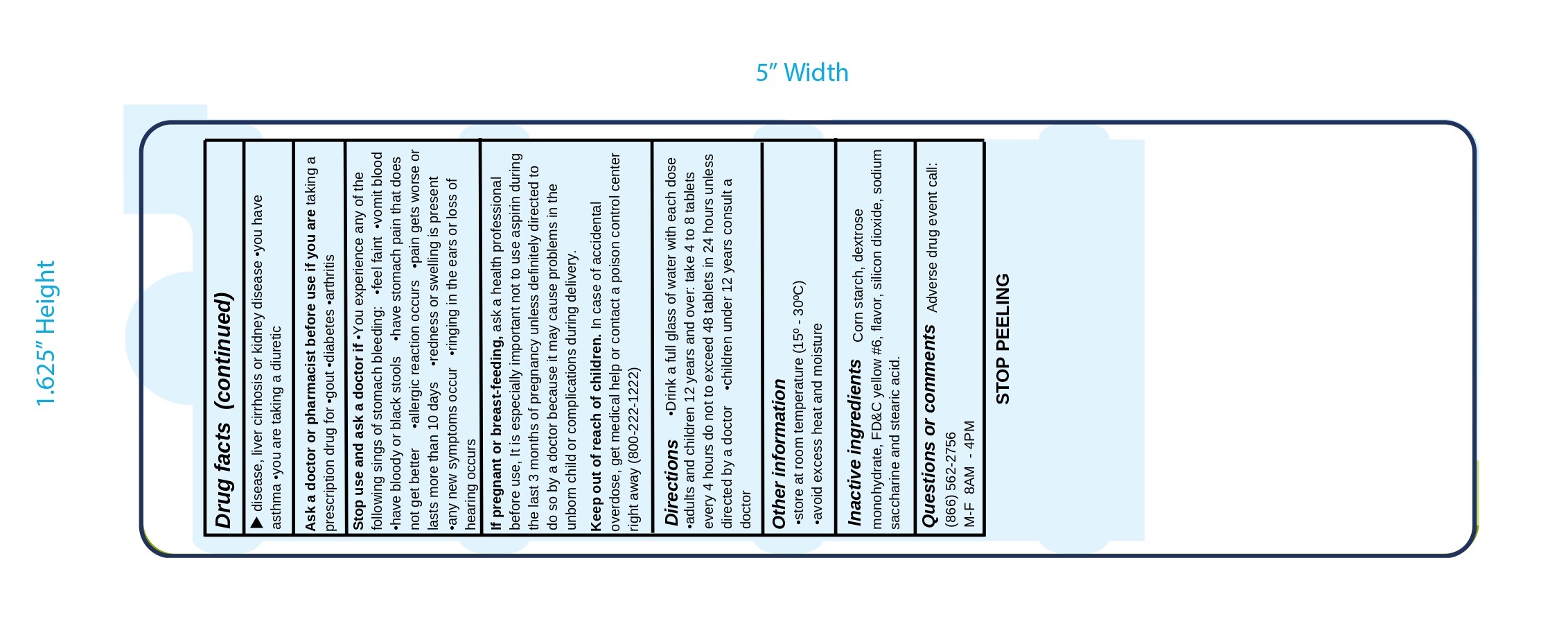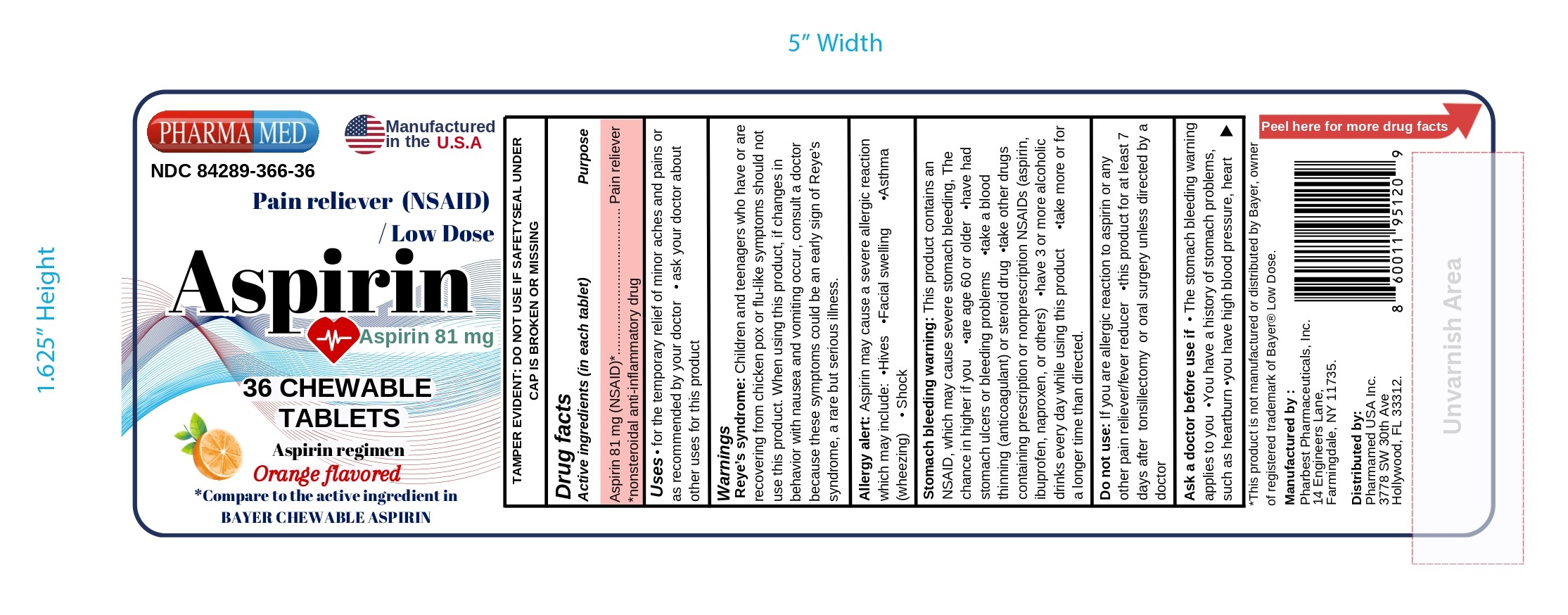 DRUG LABEL: Pain Reliever / Low Dose Aspirin
NDC: 84289-366 | Form: TABLET, CHEWABLE
Manufacturer: PHARMAMED USA INC
Category: otc | Type: HUMAN OTC DRUG LABEL
Date: 20260212

ACTIVE INGREDIENTS: ASPIRIN 81 mg/1 1
INACTIVE INGREDIENTS: SACCHARIN SODIUM; STEARIC ACID; FD&C YELLOW NO. 6; SILICON DIOXIDE; STARCH, CORN; DEXTROSE MONOHYDRATE

ASPIRIN 81mg Chewable Tablets

Active ingredient (in each tablet)

Aspirin 81mg (NSAID)*

*nonsteroidal anti-inflammatory drug

Purpose

Pain reliever

Uses

- for the temporary relief of minor aches and pains or as recommended by your doctor
- ask your doctor about other uses for this product

Warnings

Reye's syndrome: Children and teenagers who have or are recovering from chicken pox or flu-like symptoms should not use this product. When using this product, if changes in behavior with nausea and vomiting occur, consult a doctor because these symptoms could be an early sign of Reye's syndrome, a rare but serious illness.

Allergy alert: Aspirin may cause a severe alergic reaction which may include:

- hives
- facial swelling
- asthma (wheezing)
- shock

Stomach bleeding warning: This product contains an NSAID, which may cause severe stomach bleeding. The chance is higher if you:

- are age 60 or older
- have had stomach ulcers or bleeding problems
- take a blood thinning (anticoagulant) or steroid drug
- take other drugs containing prescription or nonprescription NSAIDs (aspirin, ibuprofen, naproxen, or others)
- have 3 or more alcoholic drinks every day while using this product
- take more or for a longer time than directed

Do not use

- if you are alergic to aspirin or any other pain reliever/fever reducer
- this product for at least 7 days after tonsilectomy or oral surgery unless directed by a doctor
- if you have allergic reaction to this product or any of its ingredients

Ask a doctor before use if

- stomach bleeding warning applies to you
- you have a history of stomach problems such as heartburn
- you have high blood pressure, heart disease, liver cirrhosis or kidney disease
- you have asthma
- you are taking a diuretic

Ask a doctor or pharmacist before use if you are

taking a prescription drug for

- gout
- diabetes
- arthritis

Stop use and ask a doctor if

- you experience any of the following signs of stomach bleeding: •feel faint •vomit blood •have bloody or black stools •have stomach pain that does not get better
- allergic reaction occurs
- pain gets worse or lasts more than 10 days
- redness or swelling is present
- any new symptoms occur
- ringing in the ears or loss of hearing occurs

If pregnant or breast-feeding

ask a health professional before use. It is especially important not to use aspirin during the last 3 months of pregnancy unless definitely directed to do so by a doctor because it may cause problems in the unborn child or complications during delivery.

Keep out of reach of children.

In case of accidental overdose, get medical help or contact a Poison Control Center right away (1-800-222-1222).

Directions

- drink a full glass of water with each dose
- adults and children 12 years and over: take 4 to 8 tablets every 4 hours not to exceed 48 tablets in 24 hours unless directed by a doctor
- children under 12 years: consult a doctor

Other information

- Tamper Evident: Do not use if the safety seal under the cap is broken or missing
- Store at room temperature (15°-30°C) 59ºF- 86ºF
- Avoid excess heat and moisture

Inactive ingredients

Corn starch, dextrose monohydrate, FD&C yelow #6, flavor, silicon dioxide, sodium saccharine and stearic acid.

Questions or comments?

Adverse drug event call: (866) 562-2756 (Mon-Fri 8AM to 4PM EST)

Package Label Principal Display Panel

PHARMAMED

NDC 84289-366-36

Manufactured in the U.S.A

Pain Reliever (NSAID) / Low Dose

ASPIRIN

Aspirin 81 mg

36 CHEWABLE

Aspirin regimen

Orange Flavored

*Compare to the active ingredient in BAYER Chewable Aspirin